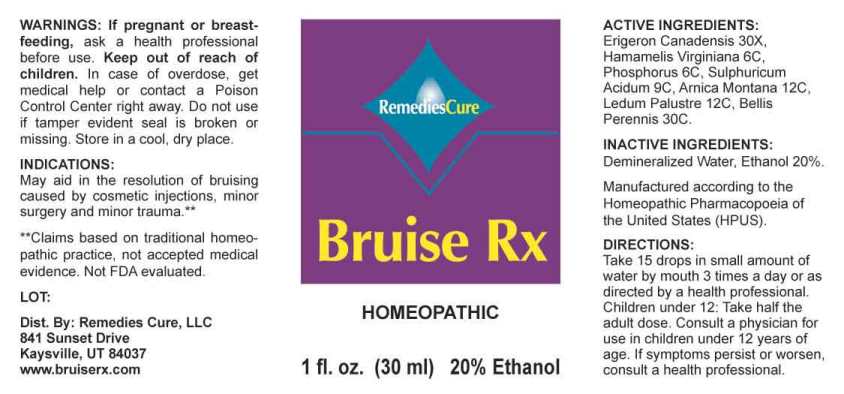 DRUG LABEL: Bruise
NDC: 82734-0001 | Form: LIQUID
Manufacturer: Remedies Cure, LLC
Category: homeopathic | Type: HUMAN OTC DRUG LABEL
Date: 20220810

ACTIVE INGREDIENTS: ERIGERON CANADENSIS WHOLE 30 [hp_X]/1 mL; HAMAMELIS VIRGINIANA ROOT BARK/STEM BARK 6 [hp_C]/1 mL; PHOSPHORUS 6 [hp_C]/1 mL; SULFURIC ACID 9 [hp_C]/1 mL; ARNICA MONTANA WHOLE 12 [hp_C]/1 mL; RHODODENDRON TOMENTOSUM LEAFY TWIG 12 [hp_C]/1 mL; BELLIS PERENNIS WHOLE 30 [hp_C]/1 mL
INACTIVE INGREDIENTS: WATER; ALCOHOL

DRUG FACTS:

ACTIVE INGREDIENTS:

Erigeron Canadensis 30X, Hamamelis Virginiana 6C, Phosphorus 6C, Sulphuricum Acidum 9C, Arnica Montana 12C, Ledum Palustre 12C, Bellis Perennis 30C.

INDICATIONS:

May aid in the resolution of bruising caused by cosmetic injections, minor surgery and minor trauma.**

**Claims based on traditional homeopathic practice, not accepted medical evidence. Not FDA evaluated.

WARNINGS:

If pregnant or breast-feeding, ask a health professional before use.

Keep out of reach of children. In case of overdose, get medical help or contact a Poison Control Center right away.

Do not use if tamper evident seal is broken or missing.

Store in cool, dry place.

KEEP OUT OF REACH OF CHILDREN. In case of overdose, get medical help or contact a Poison Control Center right away.

DIRECTIONS:

Take 15 drops in small amounts of water by mouth 3 times a day or as directed by a health professional. Children under 12: Take half the adulf dose. Consult a physician for use in children under 12 years of age. If symptoms persist ore worsen, consult a health professional.

INDICATIONS:

May aid in the resolution of bruising caused by cosmetic injections, minor surgery and minor trauma.**

**Claims based on traditional homeopathic practice, not accepted medical evidence. Not FDA evaluated.

INACTIVE INGREDIENTS:

Demineralized Water, Ethanol 20%.

QUESTIONS:

Dist. By: Remedies Cure, LLC

841 Sunset Drive

Kaysville, UT 84037

www.bruiserx.com

PACKAGE LABEL DISPLAY:

RemediesCure

Bruise RX

HOMEOPATHIC

1 fl. oz. (30 ml)